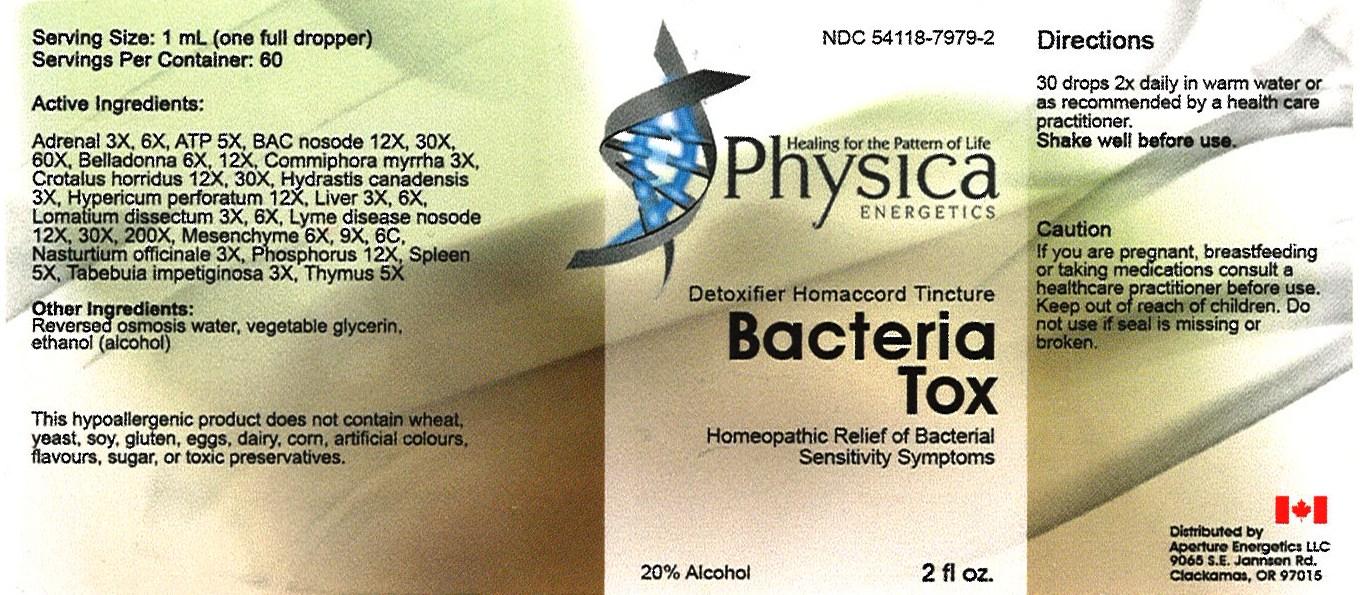 DRUG LABEL: Bacteria Tox
NDC: 54118-7979 | Form: SOLUTION/ DROPS
Manufacturer: ABCO Laboratories, Inc.
Category: homeopathic | Type: HUMAN OTC DRUG LABEL
Date: 20121130

ACTIVE INGREDIENTS: BOS TAURUS ADRENAL GLAND 3 [hp_X]/60 mL; ADENOSINE TRIPHOSPHATE 5 [hp_X]/60 mL; MYCOBACTERIUM TUBERCULOSIS 12 [hp_X]/60 mL; ATROPA BELLADONNA 6 [hp_X]/60 mL; MYRRH 3 [hp_X]/60 mL; CROTALUS HORRIDUS HORRIDUS VENOM 12 [hp_X]/60 mL; GOLDENSEAL 3 [hp_X]/60 mL; HYPERICUM PERFORATUM 12 [hp_X]/60 mL; BEEF LIVER 3 [hp_X]/60 mL; LOMATIUM DISSECTUM ROOT 3 [hp_X]/60 mL; BORRELIA BURGDORFERI 12 [hp_X]/60 mL; BOS TAURUS MESENCHYME 6 [hp_X]/60 mL; NASTURTIUM OFFICINALE 3 [hp_X]/60 mL; PHOSPHORUS 12 [hp_X]/60 mL; BOS TAURUS SPLEEN 5 [hp_X]/60 mL; TABEBUIA IMPETIGINOSA BARK 3 [hp_X]/60 mL; HUMAN THYMUS 5 [hp_X]/60 mL
INACTIVE INGREDIENTS: WATER; GLYCERIN; ALCOHOL

Bacteria Tox Homeopathic Relief

Active Ingredients:

- Adrenal 3X, 6X
- ATP 5X
- BAC nosode 12X, 30X, 60X
- Belladonna 6X, 12X
- Commiphora myrrha 3X
- Crotalus horridus 12X, 30X
- Hydrastis canadensis 3x
- Hypericum perforatum 12X
- Liver 3X, 6X
- Lomatium dissectum 3X, 6X
- Lyme disease nosode 12X, 30X, 200X
- Mesenchyme 6X, 9X, 6C
- Nasturtium officinale 3X
- Phosphorus 12X
- Spleen 5X
- Tabebuia impetiginosa 3X
- Thymus 5X

PURPOSE

Detoxifier Homaccord Tincture

Homeopathic Relief of Bacterial Sensitivity Symptoms

Keep out of reach of children

INDICATIONS AND USAGE

- 30 drops 2X daily in warm water
- or as recommended by a health care practitioner
- Shake Well before use

WARNINGS

- If you are pregnant, breastfeeding or taking medications consult a health care practitioner before use.
- Keep out of reach of children
- Do not use if seal is missing or broken

DOSAGE AND ADMINISTRATION

- 30 drops 2x daily in warm water
- or as recommended by a health care practitioner
- Shake well before use.

INACTIVE INGREDIENT

Reverse osmosis water
Vegetabe glycerin
Alcohol (ethanol)

PACKAGE LABEL

- bacteriatoxlabel.jpg
- image of bottle label